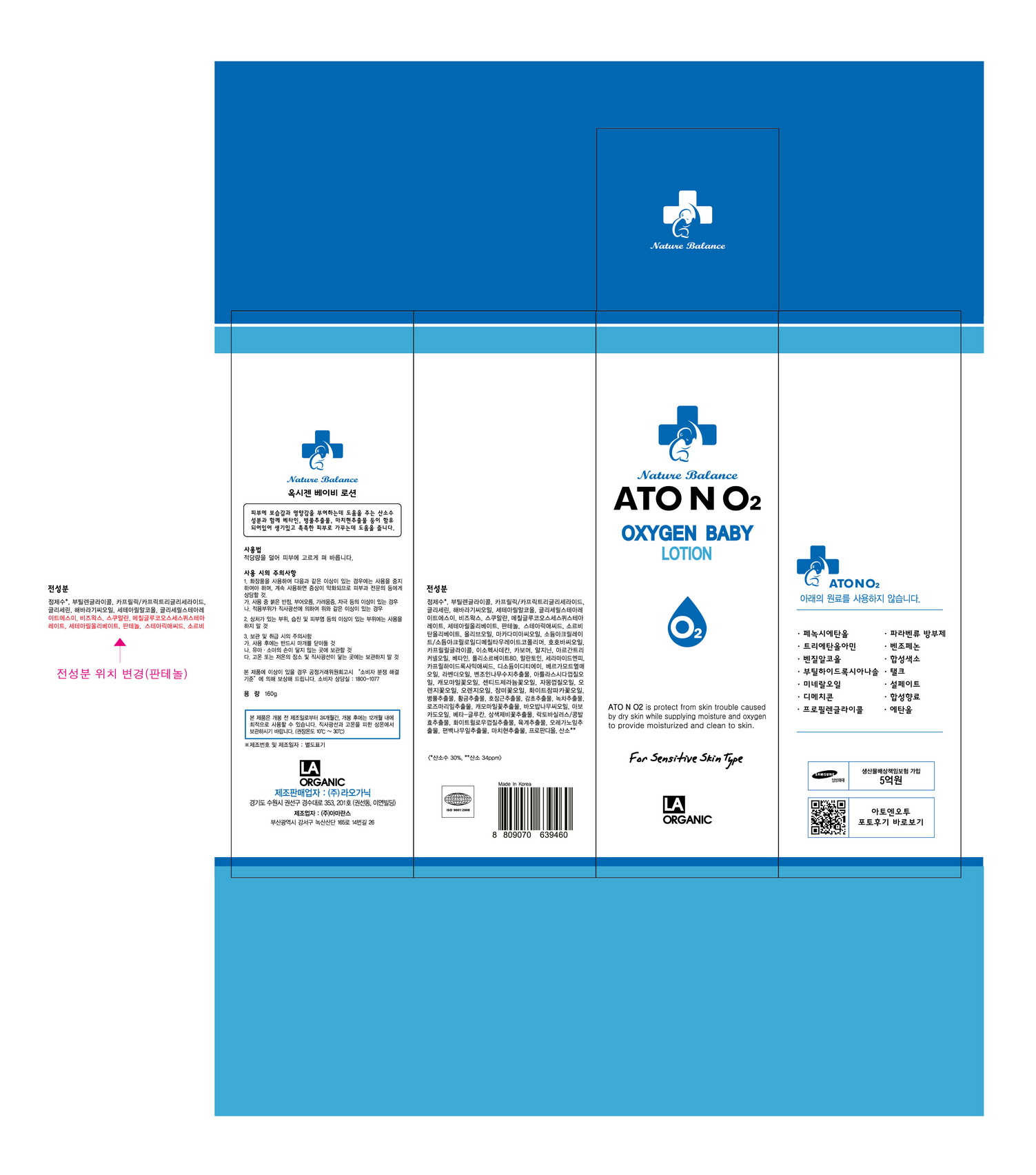 DRUG LABEL: ATONO2 Oxygen Baby
NDC: 70993-0005 | Form: LOTION
Manufacturer: LAORGANIC Co., Ltd.
Category: otc | Type: HUMAN OTC DRUG LABEL
Date: 20161013

ACTIVE INGREDIENTS: BETAINE 0.2 g/100 g
INACTIVE INGREDIENTS: WATER; GLYCERIN

Drug Facts

ACTIVE INGREDIENT

Betaine

INACTIVE INGREDIENT

Water, Glycerin, Centella Asiatica Extract, Portulaca Oleracea Extract, etc.

PURPOSE

Skin Protectant

keep out of reach of the children

INDICATIONS AND USAGE

Apply proper amount to the skin

WARNINGS

- For external use only
- When using this product

1. If any one of following symptoms occurs when using cosmetics, stop using it and consult a dermatologist.
A. red spot, swelling, itching, stimulus
B. symptoms mentioned above are caused by sunlight.

2. Do not apply on skin where there is wound, eczema, or irritation.

3. Storage and cautions for handling
A. Close stopper after using.
B. Keep out of reach of children.
C. Keep away from high or low temperature and direct sunlight.

4. This is not a medicinal product. Made of 100% cosmetic ingredients, it is a sensitive-skin care product for all skin types.

DOSAGE AND ADMINISTRATION

for external use only